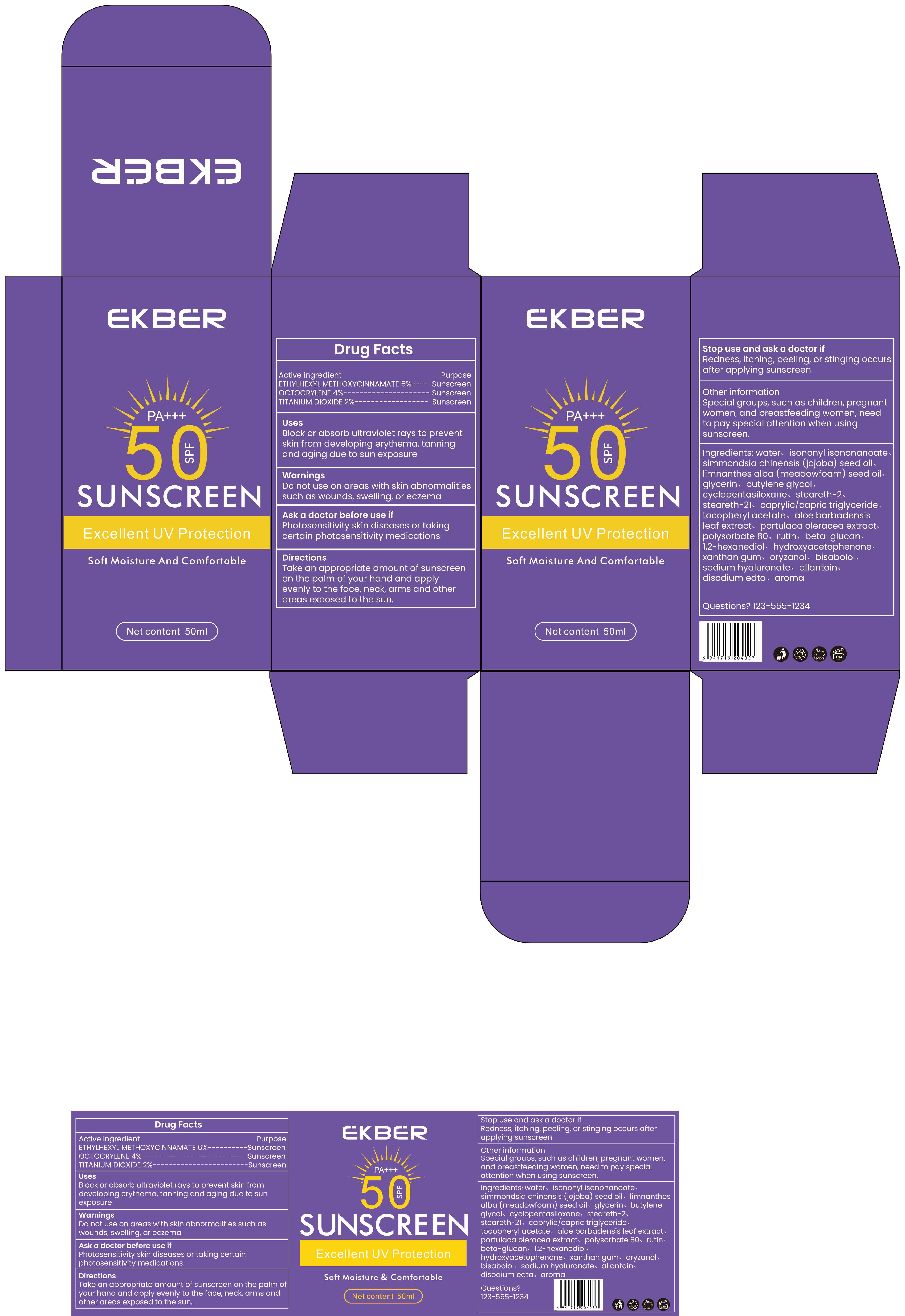 DRUG LABEL: SUNSCREEN SPF50
NDC: 85998-001 | Form: CREAM
Manufacturer: Guangzhou Tinsun Biotechnology Company Limited
Category: otc | Type: HUMAN OTC DRUG LABEL
Date: 20250807

ACTIVE INGREDIENTS: OCTOCRYLENE 4 g/100 mL; TITANIUM DIOXIDE 2 g/100 mL; ETHYLHEXYL METHOXYCINNAMATE 6 g/100 mL
INACTIVE INGREDIENTS: ISONONYL ISONONANOATE; GLYCERIN; AROMATIC-L-AMINO-ACID DECARBOXYLASE; .ALPHA.-TOCOPHEROL ACETATE; RUTIN; SODIUM CARBOXYMETHYL .BETA.-GLUCAN (DS 0.65-0.85); 1,2-HEXANEDIOL; HYDROXYACETOPHENONE; XANTHAN GUM; ORYZANOL; SODIUM HYALURONATE; ALLANTOIN; EDETATE DISODIUM; STEARETH-2; WATER; LIMNANTHES ALBA (MEADOWFOAM) SEED OIL; STEARETH-21; CAPRYLIC/CAPRIC TRIGLYCERIDE; BUTYLENE GLYCOL; ALOE BARBADENSIS LEAF; PURSLANE; BISABOLOL; CYCLOPENTASILOXANE; POLYSORBATE 80; SIMMONDSIA CHINENSIS (JOJOBA) SEED OIL

85998-001 SUNSCREEN SPF50

ACTIVE INGREDIENT

ETHYLHEXYL METHOXYCINNAMATE 6%
OCTOCRYLENE 4%
TITANIUM DIOXIDE 2%

PURPOSE

Sunscreen

INDICATIONS AND USAGE

Block or absorb ultraviolet rays to preventskin from developing erythema, tanningand aging due to sun exposure

Do not use on areas with skin abnormalitiessuch as wounds, swelling, or eczemd

Do not use on areas with skin abnormalitiessuch as wounds, swelling, or eczemd

Ask a doctor before use if
Photosensitivity skin diseases or taking certain photosensitivity medications

Stop use and ask a doctor if
Redness,itching, peeling, or stinging occurs after applying sunscreen

KEEP OUT OF REACH OF CHILDREN SECTION

DOSAGE AND ADMINISTRATION

Take an appropriate amount of sunscreenon the palm of your hand and applyevenly to the face, neck, arms and otherareas exposed to the sun.

INACTIVE INGREDIENT

WATER
ISONONYL ISONONANOATE
SIMMONDSIA CHINENSIS (JOJOBA) SEED OIL
LIMNANTHES ALBA (MEADOWFOAM) SEED OIL
GLYCERIN
BUTYLENE GLYCOL
CYCLOPENTASILOXANE
STEARETH-2
STEARETH-21
CAPRYLIC/CAPRIC TRIGLYCERIDE
TOCOPHERYL ACETATE
ALOE BARBADENSIS LEAF EXTRACT
PORTULACA OLERACEA EXTRACT
POLYSORBATE 80
RUTIN
BETA-GLUCAN
1,2-HEXANEDIOL
HYDROXYACETOPHENONE
XANTHAN GUM
ORYZANOL
BISABOLOL
SODIUM HYALURONATE
ALLANTOIN
DISODIUM EDTA
AROMA